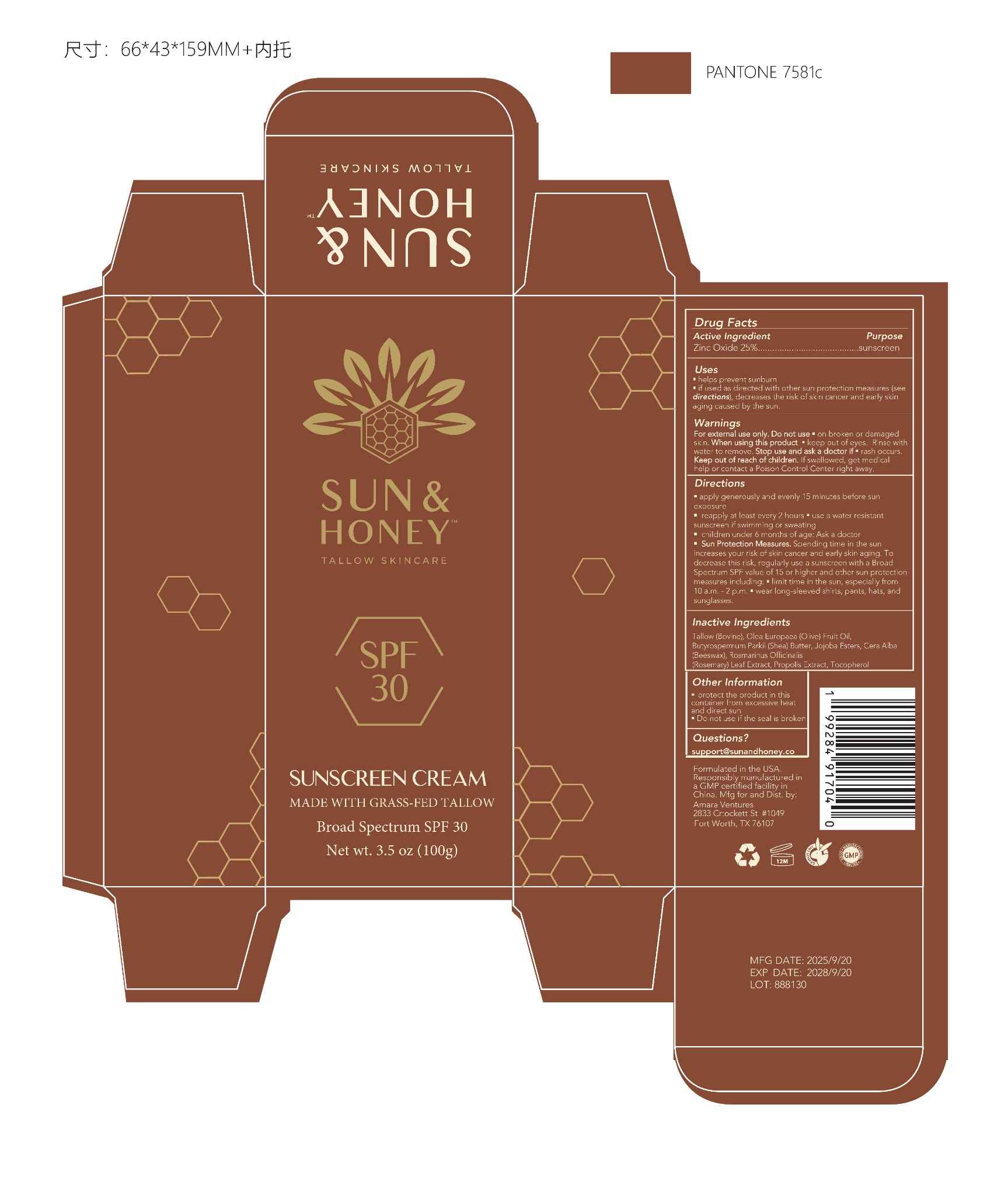 DRUG LABEL: Sun and Honey Tallow Sunscreen SPF 30
NDC: 85432-002 | Form: CREAM
Manufacturer: Amara Ventures
Category: otc | Type: HUMAN OTC DRUG LABEL
Date: 20250915

ACTIVE INGREDIENTS: ZINC OXIDE 250 mg/1 g
INACTIVE INGREDIENTS: BEEF TALLOW; OLIVE OIL; SHEA BUTTER; ROSEMARY OIL; TOCOPHEROL; BEESWAX; SIMMONDSIA CHINENSIS (JOJOBA) SEED WAX; PROPOLIS CERA

Active Ingredient

Zinc Oxide 25%

Purpose

sunscreen

Uses

• helps prevent sunburn
• if used as directed with other sun protection measures (see directions), decreases the risk of skin cancer and early skin aging caused by the sun

Warnings

For external use only.

Do not use
• on broken or damaged skin

When using this product
• keep out of eyes. Rinse with water to remove

Stop use and ask a doctor if
• rash occurs

Keep out of reach of children. If swallowed, get medical help or contact a Poison Control Center right away.

Directions

• apply generously and evenly 15 minutes before sun exposure
• reapply at least every 2 hours
• use a water resistant sunscreen if swimming or sweating
• children under 6 months of age: ask a doctor
• Sun Protection Measures. Spending time in the sun increases your risk of skin cancer and early skin aging. To decrease this risk, regularly use a sunscreen with a Broad Spectrum SPF value of 15 or higher and other sun protection measures including:

- limit time in the sun, especially from 10 a.m. – 2 p.m.
- wear long-sleeved shirts, pants, hats, and sunglasses

Inactive Ingredients

Tallow (Bovine), Olea Europaea (Olive) Fruit Oil, Butyrospermum Parkii (Shea) Butter, Jojoba Esters, Cera Alba (Beeswax), Rosmarinus Officinalis (Rosemary) Leaf Extract, Propolis Extract, Tocopherol

Other Information

- protect the product in this container from excessive heat and direct sun
- Do not use if the seal is broken

Questions?

support@sunandhoney.co